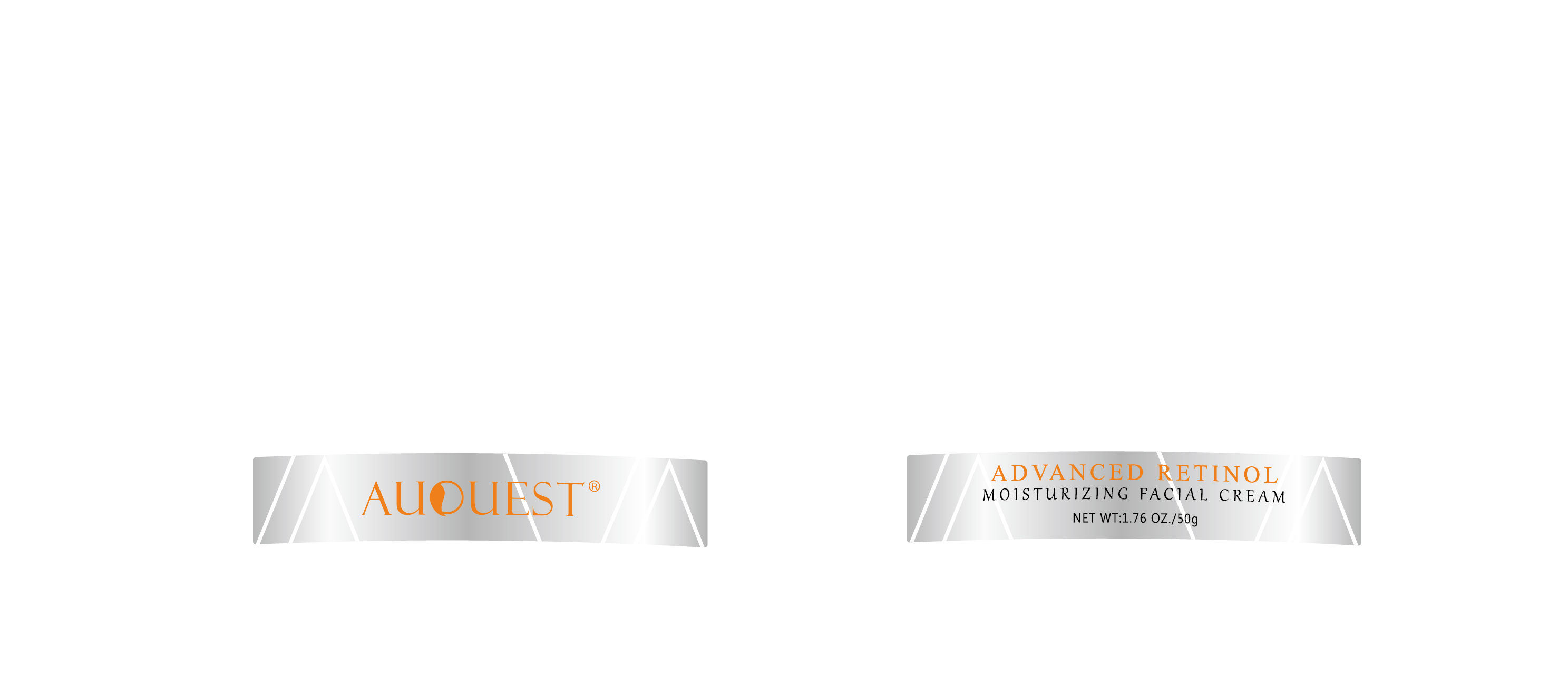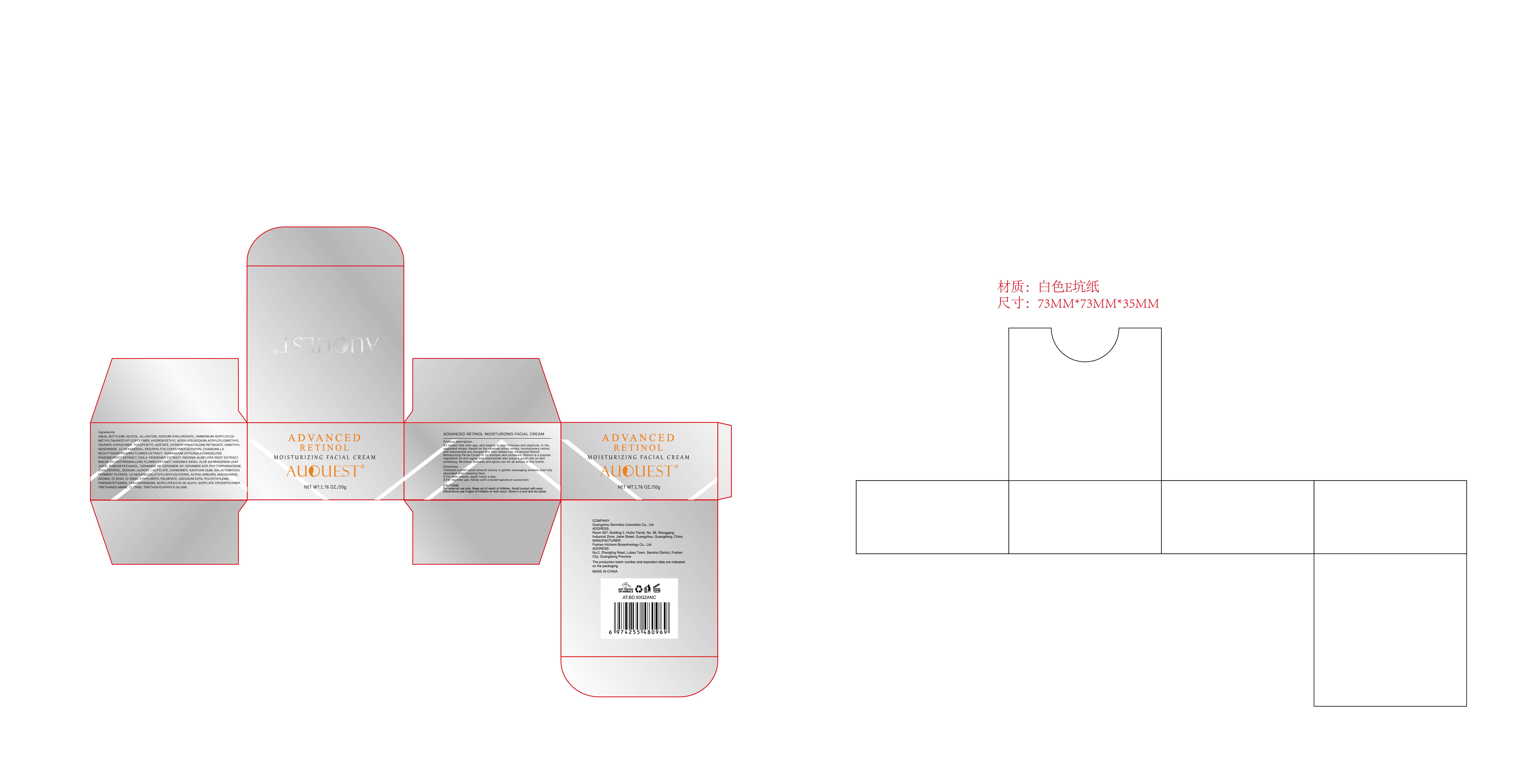 DRUG LABEL: Auquest Advancedretinol Moisturizing Facial Cream
NDC: 84186-014 | Form: CREAM
Manufacturer: Guangzhou Bonnieco Cosmetics Co., Ltd
Category: otc | Type: HUMAN OTC DRUG LABEL
Date: 20240409

ACTIVE INGREDIENTS: 2-BUTYNE-1,4-DIOL 10 g/100 g
INACTIVE INGREDIENTS: PTEROPTERIN; FD&C YELLOW NO. 5; EDETATE DISODIUM; ETHYLHEXYL PALMITATE; WATER; MALVA SYLVESTRIS FLOWER; PHENOXYETHANOL; HYDROXYPINACOLONE RETINOATE; PAEONIA LACTIFLORA ROOT; HIGH DENSITY POLYETHYLENE; DIMETHYL ISOSORBIDE; 1,2-HEXANEDIOL; CHAMOMILE; DIHYDROXYISOPROPYL PALMOYLPALMAMIDE; PHYTOSPHINGOSINE; CARBOMER HOMOPOLYMER, UNSPECIFIED TYPE; TROLAMINE; TRIETHOXYCAPRYLYLSILANE; TARAXACUM OFFICINALE; NIACINAMIDE; ACRYLATES/C10-30 ALKYL ACRYLATE CROSSPOLYMER (60000 MPA.S); FERRIC OXIDE YELLOW; CERAMIDE NP; CHLORPHENESIN; ETHYLHEXYLGLYCERIN; FD&C YELLOW NO. 6; CHOLESTEROL; ALPHA-ARBUTIN; HYALURONATE SODIUM; METHYL HEXYL ETHER; LUPINUS KINGII WHOLE; SODIUM LAUROYL LACTYLATE; ALLANTOIN; AMMONIUM ACRYLOYLDIMETHYLTAURATE/VP COPOLYMER; HYDROXYETHYL ACRYLATE/SODIUM ACRYLOYLDIMETHYL TAURATE COPOLYMER (45000 MPA.S AT 1%); .ALPHA.-TOCOPHEROL ACETATE; ALOE VERA LEAF; CERAMIDE AP; GEOTRICHUM CANDIDUM; PEG/PPG-17/6 COPOLYMER; GLYCERIN; XANTHAN GUM; SURFOMER

84186-014

Active Ingredient

BUTYLEME GLYCOLI ALLANTOIN 10%

Purpose

face (body part)

Use

1.Smooth a pearl-sized amount evenly in gentle massaging strokes until fullyabsorbed after cleaning face.
2.For best results,apply twice a day;
3.For daytime use, follow with a broad-spectrum sunscreen.

Warnings

For external use only. Keep out of reach of children.Avoid contact with eyes.Discontinue use if signs of irritation or rash occur. Store in a cool and dry place.

Do not use

It's known that with age, skin begins to lose firmness and elasticity. In theupgraded recipe, based on the existing retinol series, revolutionary retinoland niacinamide are merged and then added into Advanced Retinol，Moisturizing Facial Cream to fix multiple skin problems. Retinol is a popularingredient on anti-aging and niacinamide also plays a good role on skinwhitening. Wrinkles, dullness and spots can be all solved in this bottle.

When Using

In case of contact with the eyes, rinse immediately with plenty of water.

Stop Use

If discomfort arises, please immediately stop using the product and seek the assistance of a dermatologist.

Ask Doctor

If discomfort arises, please immediately stop using the product and seek the assistance of a dermatologist.

Keep Oot Of Reach Of Children

Directions

1.Smooth a pearl-sized amount evenly in gentle massaging strokes until fullyabsorbed after cleaning face.
2.For best results,apply twice a day;
3.For daytime use, follow with a broad-spectrum sunscreen.

Inactive ingredients

AQUA, SODIUM HYALURONATE,AMMONIUM ACRYLOYLDl-METHYLTAURATE/VP COPOLYMER, HYDROXYETHYL ACRYLATE/SODIUM ACRYLOYLDIMETHYLTAURATE COPOLYMER,TOCOPHETYL ACETATE, HYDROXYPINACOLONE RETINOATE, DIMETHYLISOSORBIDE, 1,2-HEXANEDIOL,PEG/PPG-17/6 COPOLYMER,GLYCERIN CHAMOMILLA RECUTITA(MATRICARIA) FLOWER EXTRACT, TARAXACUM OFFICINALE(DANDELION) RHIZOME/ROOT EXTRACT, CIOLA YEDOENSIS EXTRACT, PAEONIA ALBIFLORA ROOT EXTRACT,MALVA SYLVESTRIS(MALLOW)FLOWER EXTRACT, KlNGINKA EKISU, ALOE BARBADENSIS LEAFJUICE, PHENOXYETHANOL,CERAMIDE NP, CERAMIDE AP, CERAMIDE EOP,PHYTOSPHINGOSINE,CHOLESTEROL, SODIUM LAUROYLLACTYLATE,CARBOMER,XANTHAN GUM,GALACTOMYCESFERMENT FILTRATE,1,2-HEXANEDIOL,ETHYLHEXYLGLYCERIN, ALPHA-ARBURIN,NIACINAMIDE,AROMA, CI 19140, CI 15985,ETHYLHEXYL PALMITATE, DISODIUM EDTA, POLYETHYLEME, PHENOXYETHANOL, CHLORPHENESIN, ACRYLATES/C10-30 ALKYL ACRYLATE CROSSPOLYMER,TRIETHANOLAMINE,CL77492,TRIETHOXYCAPRYLYLSILANE